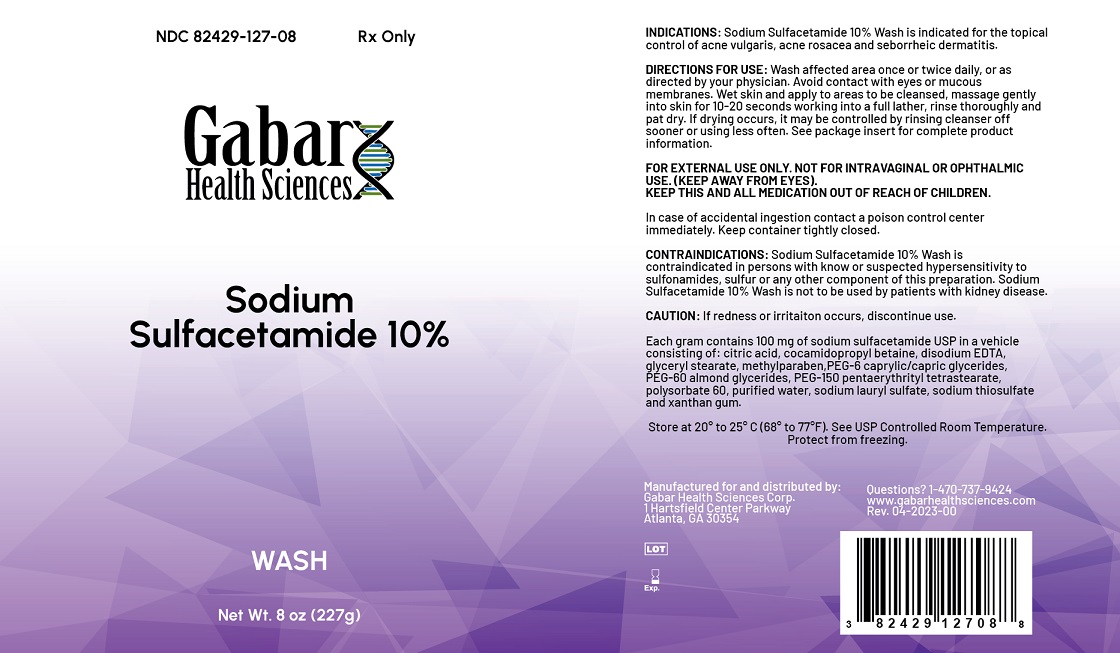 DRUG LABEL: Sodium Sulfacetamide Wash 10%
NDC: 82429-127 | Form: LIQUID
Manufacturer: Gabar Health Sciences Corp.
Category: prescription | Type: HUMAN PRESCRIPTION DRUG LABEL
Date: 20240129

ACTIVE INGREDIENTS: SULFACETAMIDE SODIUM 100 mg/1 g
INACTIVE INGREDIENTS: CITRIC ACID MONOHYDRATE; COCAMIDOPROPYL BETAINE; EDETATE DISODIUM; GLYCERYL MONOSTEARATE; METHYLPARABEN; CAPRYLOCAPROYL POLYOXYLGLYCERIDES 6; PEG-60 ALMOND GLYCERIDES; PEG-150 PENTAERYTHRITYL TETRASTEARATE; POLYSORBATE 60; WATER; SODIUM LAURYL SULFATE; SODIUM THIOSULFATE; XANTHAN GUM

Sodium Sulfacetamide Wash 10%

INDICATIONS AND USAGE

INDICATIONS: Sodium Sulfacetamide 10% Wash is intended for topical application in the following scaling dermatoses: seborrheic dermatitis and seborrhea sicca (dandruff). It also is indicated for the treatment of secondary bacterial infections of the skin due to organisms susceptible to sulfonamides.

DOSAGE AND ADMINISTRATION

DIRECTIONS FOR USE: Wash affected areas twice daily(morning and evening) or as directed by your physician. Rinse thoroughly and pat dry. See package insert for complete product information.

WARNINGS

FOR EXTERNAL USE ONLY. NOT FOR INTRAVAGINAL OR OPHTHALMIC USE. (KEEP AWAY FROM EYES).

WARNINGS

KEEP THIS AND ALL MEDICATION OUT OF REACH OF CHILDREN.

In case of accidental ingestion contact a poison control center immediately. Keep container tightly closed.

CONTRAINDICATIONS

CONTRAINDICATIONS:Sodium Sulfacetamide 10% Wash is contraindicated in persons with known or suspected hypersensitivity to sulfonamides.

INACTIVE INGREDIENT

Each gram contains 100 mg of sodium sulfacetamide USP in a vehicle consisting of: citric acid, cocamidopropyl betaine, disodium EDTA, glyceryl stearate, methylparaben, PEG-6 caprylic/capric glycerides, PEG-60 almond glycerides, PEG-150 pentaerythrityl tetrastearate, polysorbate 60, purified water, sodium lauryl sulfate, sodium thiosulfate and xanthan gum.

STORAGE AND HANDLING

Store at 25°C (77°F); excursions permitted to 15 to 30°C (59 to 86°F). See USP Controlled Room. Protect from freezing.

See bottle for lot number and expiration date.

Manufactured for and distributed by:
Gabar Health Sciences Corp
Atlanta, GA 30354

Adverse Reaction

Although rare, sodium sulfacetamide may cause local irritation.

Call your doctor for medical advice about side effects.

To report a serious adverse event or obtain product information, call 1-470-737-9424.

PACKAGE LABEL

SODIUM SULFACETAMIDE 10% WASH

(sodium sulfacetamide 10%)

Rx Only

FOR EXTERNAL USE ONLY.

NOT FOR OPHTHALMIC USE.

Description: Each gram contains 100 mg of sodium sulfacetamide USP in a vehicle consisting of: citric acid, cocamidopropyl betaine, disodium EDTA, glyceryl stearate, methylparaben, PEG-6 caprylic/capric glycerides, PEG-60 almond glycerides, PEG-150 pentaerythrityl tetrastearate, polysorbate 60, purified water, sodium lauryl sulfate, sodium thiosulfate and xanthan gum.

HOW SUPPLIED: Sodium Sulfacetamide Wash 10% is available in a 8 fl oz (227g) bottle, NDC 82429-127-08.

Manufactured for and distributed by Gabar Health Sciences Corp.

Atlanta, GA 30354

Rev 4/23